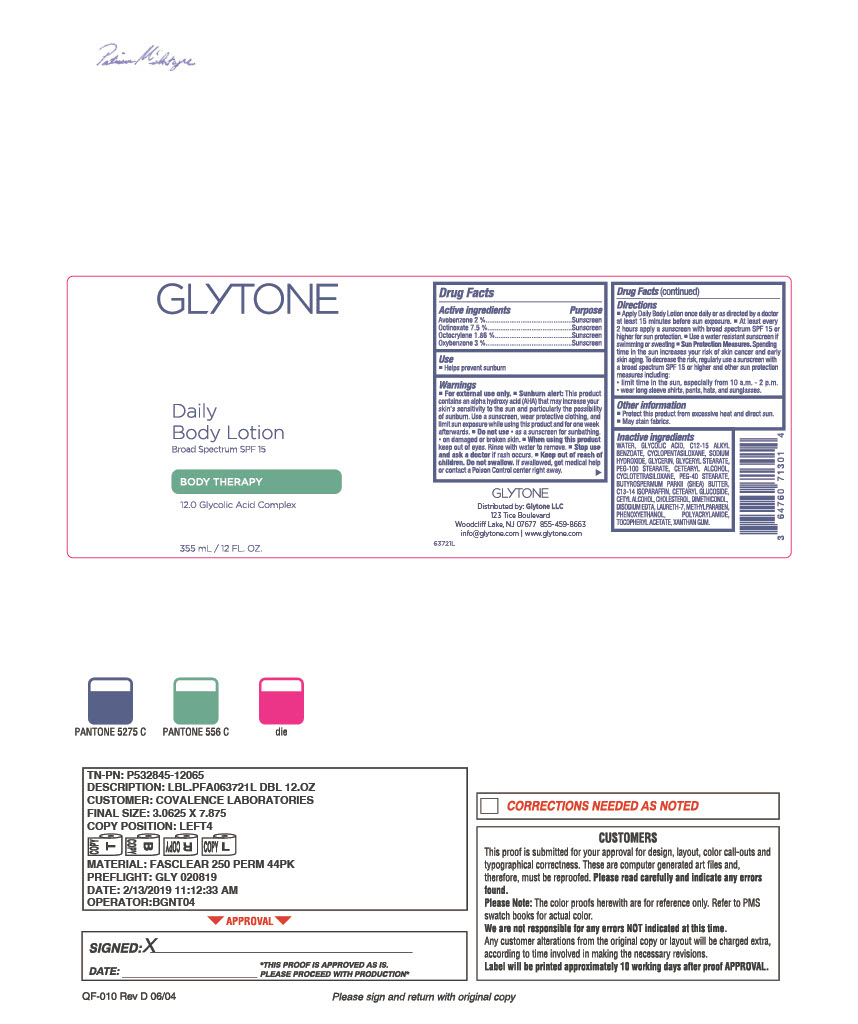 DRUG LABEL: Glytone Daily Body
NDC: 84262-027 | Form: LOTION
Manufacturer: Glytone, LLC
Category: otc | Type: HUMAN OTC DRUG LABEL
Date: 20250623

ACTIVE INGREDIENTS: AVOBENZONE 2 g/100 g; OCTINOXATE 7.5 g/100 g; OCTOCRYLENE 1.86 g/100 g; OXYBENZONE 3 g/100 g
INACTIVE INGREDIENTS: BUTYROSPERMUM PARKII (SHEA) BUTTER; TRIETHANOLAMINE; WATER; GLYCERIN; GLYCERYL STEARATE; PEG-100 STEARATE; ALOE BARBADENSIS LEAF JUICE; CARBOMER; TOCOPHERSOLAN; FRAGRANCE 13576; EDETATE DISODIUM; C12-15 ALKYL BENZOATE; DIMETHICONE; ETHYLHEXYLGLYCERIN; CETYL ALCOHOL; PHENOXYETHANOL

INDICATIONS AND USAGE

Helps prevent sunburn.

DOSAGE AND ADMINISTRATION

Apply Daily Body Lotion once daily or as directed by a doctor at least 15 minutes before sun exposure.
Reapply at least every 2 hours. Use a water resistant sunscreen if swimming or sweating.

PURPOSE

Avobenzone 2% – Sunscreen
Octinoxate 7.5% – Sunscreen
Octocrylene 1.86% – Sunscreen
Oxybenzone 3% – Sunscreen

WARNINGS

For external use only.
Sunburn alert: This product contains an alpha hydroxy acid (AHA) that may increase your skin’s sensitivity to the sun and particularly the possibility of sunburn. Use a sunscreen, wear protective clothing, and limit sun exposure while using this product and for one week afterwards.

Do not use:
- on damaged or broken skin.
- as a sunscreen for sunbathing.

When using this product:
- keep out of eyes. Rinse with water to remove.

Stop use and ask a doctor if:
- rash occurs.

Keep out of reach of children.
Do not swallow. If swallowed, get medical help or contact a Poison Control Center right away.

INACTIVE INGREDIENT

Water, Glycolic Acid, C12-15 Alkyl Benzoate, Cyclopentasiloxane, Sodium Hydroxide, Glycerin, Glyceryl Stearate, PEG-100 Stearate, Cetearyl Alcohol, Cyclotetrasiloxane, PEG-40 Stearate, Butyrospermum Parkii (Shea) Butter, C13-14 Isoparaffin, Cetearyl Glucoside, Cetyl Alcohol, Cholesterol, Dimethiconol, Disodium EDTA, Laureth-7, Methylparaben, Phenoxyethanol, Polyacrylamide, Tocopheryl Acetate, Xanthan Gum.

RECENT MAJOR CHANGES

deleted undefined photo

Keep out of reach of children. If swallowed, get medical help or contact a Poison Control Center right away